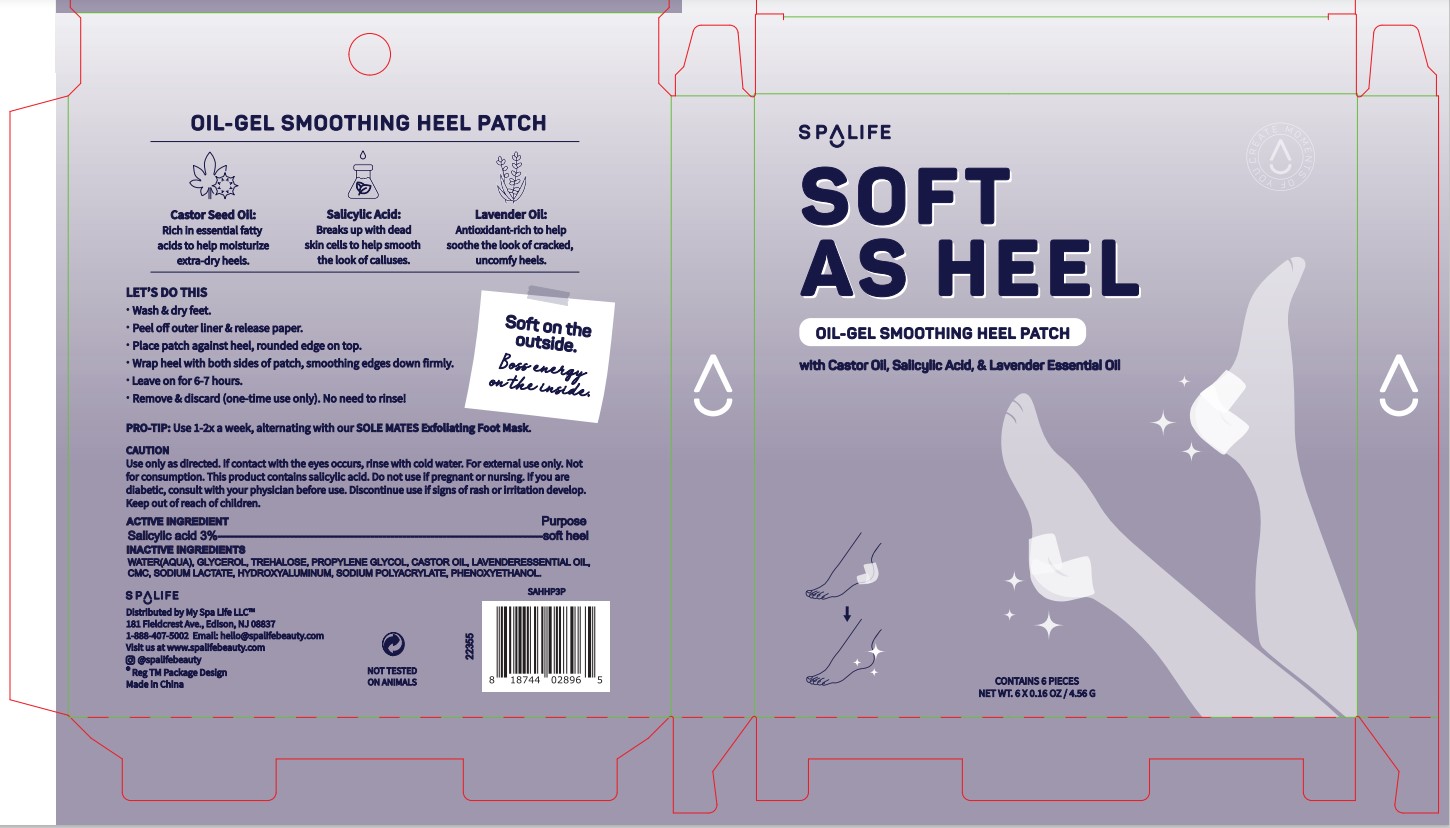 DRUG LABEL: Spalife Soft As Heel Oil-Gel smoothing Heel Patch
NDC: 69139-601 | Form: SWAB
Manufacturer: YIWU HAODING MEDICAL CO.,LTD
Category: otc | Type: HUMAN OTC DRUG LABEL
Date: 20230313

ACTIVE INGREDIENTS: SALICYLIC ACID 3 g/100 g
INACTIVE INGREDIENTS: WATER; TREHALOSE; PROPYLENE GLYCOL; CASTOR OIL; SODIUM LACTATE; PHENOXYETHANOL

Active Ingredients

Salicylic acid 3%

Purpose

soft heel

Use

soft heel

Warnings

For external use only.

Use only as directed. If contact with the eyes occurs, rinse with cold water.

Not for consumptiohn

Do not use if pregnant or nursing.

If you are diabetic, consult with your physician before use.

Discontinue use if signs Of irriation develop.

KEEP OUT OF REACH OF CHILDREN

if swallowed, get medical help or contact Poison control Center right away.

Do not use if you are gregnant.

Discontinue use if signs Of irriation develop.

Directions

- Wash and dry feet
- Peel off outer liner and release paper.
- Place patch against heel, round edge on top.
- Wrap heel with both sides of patch, smoothing edges down firmly
- Leave on for 6-7 hours.
- Remove & Discard (one-time use only). No need to rinse!

Inactive Ingredient

water, Glycerol, Trehalose, Propylene Glycol, Castor Oil, Lavenderessential Oil, CMC, Sodium Lactate, Hydroxyaluminum,Sodium Polyacrylate, Phenoxyethanol